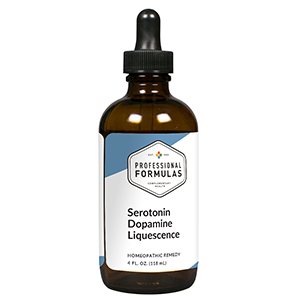 DRUG LABEL: Serotonin Dopamine Liquescence
NDC: 63083-3019 | Form: LIQUID
Manufacturer: Professional Complementary Health Formulas
Category: homeopathic | Type: HUMAN OTC DRUG LABEL
Date: 20190815

ACTIVE INGREDIENTS: CHOLINE 3 [hp_X]/118 mL; INOSITOL 3 [hp_X]/118 mL; MAGNESIUM PHOSPHATE, DIBASIC TRIHYDRATE 3 [hp_X]/118 mL; MEDICAGO SATIVA WHOLE 3 [hp_X]/118 mL; MUSA X PARADISIACA FLOWER 3 [hp_X]/118 mL; SCUTELLARIA LATERIFLORA WHOLE 3 [hp_X]/118 mL; VALERIAN 3 [hp_X]/118 mL; .GAMMA.-AMINOBUTYRIC ACID 4 [hp_X]/118 mL; NERIUM OLEANDER WHOLE 4 [hp_X]/118 mL; SUS SCROFA PINEAL GLAND 6 [hp_X]/118 mL; BOS TAURUS PITUITARY GLAND, POSTERIOR 6 [hp_X]/118 mL; CADMIUM 12 [hp_X]/118 mL; UBIDECARENONE 12 [hp_X]/118 mL; PHOSPHATIDYL SERINE 12 [hp_X]/118 mL; DOPAMINE 12 [hp_X]/118 mL; SEROTONIN 12 [hp_X]/118 mL
INACTIVE INGREDIENTS: ALCOHOL; WATER

T19

ACTIVE INGREDIENTS

Choline 3X
Inositol 3X
Magnesia phosphorica 3X
Medicago sativa 3X
Musa sapientum 3X
Scutellaria lateriflora 3X
Valeriana officinalis 3X
GABA 4X
Oleander 4X
Pineal 6X
Pituitary 6X
Cadmium metallicum 12X
Coenzyme Q10 12X
Phosphatidylserine 12X
Dopamine 12X, 16X
Serotonin 12X, 16X

QUESTIONS

Professional Formulas

PO Box 2034 Lake Oswego, OR 97035

INDICATIONS

For the temporary relief of anxiousness, restlessness, feelings of sadness, excessive worry, poor concentration, or stress.*

PURPOSE

*Claims based on traditional homeopathic practice, not accepted medical evidence. Not FDA evaluated.

WARNINGS

In case of overdose, get medical help or contact a poison control center right away.

Keep out of the reach of children.

PREGNANCY OR BREAST FEEDING

If pregnant or breastfeeding, ask a healthcare professional before use.

DIRECTIONS

Place drops under tongue 30 minutes before/after meals. Adults and children 12 years and over: Take one full dropper up to 2 times per day. Consult a physician for use in children under 12 years of age.

OTHER INFORMATION

Tamper resistant. If seal is broken, do not use. After opening, close container tightly and store at room temperature away from heat.

INACTIVE INGREDIENTS

20% ethanol, purified water.

LABEL

Est 1985

Professional Formulas

Complementary Health

Serotonin Dopamine Liquescence

Homeopathic Remedy

4 FL. OZ. (118 mL)